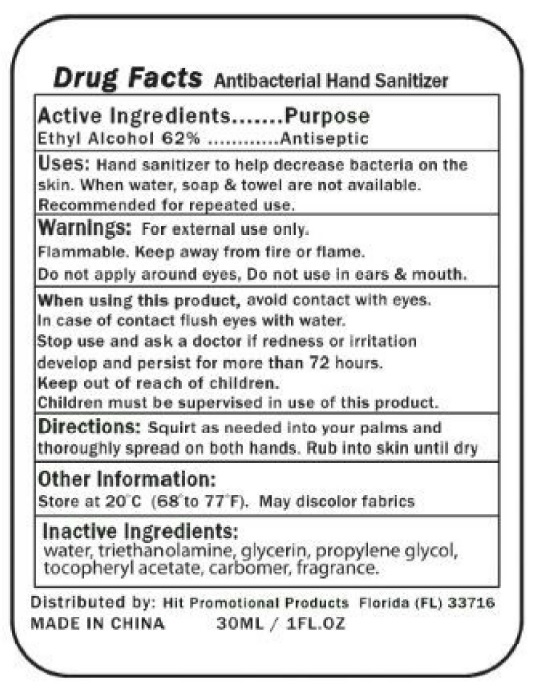 DRUG LABEL: Antibacterial Hand Sanitizer
NDC: 70204-100 | Form: GEL
Manufacturer: Hit Promotional Products
Category: otc | Type: HUMAN OTC DRUG LABEL
Date: 20231121

ACTIVE INGREDIENTS: ALCOHOL 620 mg/1 mL
INACTIVE INGREDIENTS: WATER; TROLAMINE; GLYCERIN; PROPYLENE GLYCOL; .ALPHA.-TOCOPHEROL ACETATE

Antibacterial Hand Sanitizer

Active Ingredients

Ethyl Alcohol 62%

Purpose

Antiseptic

Uses:

Hand sanitizer to help decrease bacteria on the skin. When water, soap & towel are not available. Recommended for repeated use.

Warnings:

For external use only. Flammable. Keep away from fire or flame. Do not apply around eyes.

Do not use

in ears & mouth.

When using this product,

avoid contact with eyes. In case of contact flush eyes with water.

Stop use and ask a doctor

if redness or irritation develop and persist for more than 72 hours.

Keep out of reach of children.

Children must be supervised in use of this product.

Directions:

Squirt as needed into your palms and thoroughly spread on both hands. Rub into skin until dry

Other Information:

Store at 20oC (68o to 77oF). May discolor fabrics

Inactive Ingredients:

water, triethanolamine, glycerin, propylene glycol, tocopheryl acetate, carbomer, fragrance.